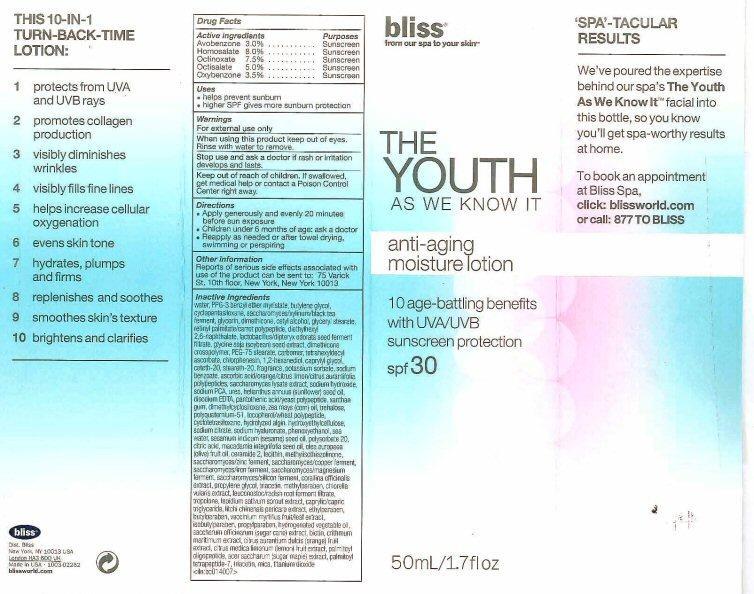 DRUG LABEL: THE YOUTH AS WE KNOW IT
NDC: 67038-110 | Form: LOTION
Manufacturer: Bliss World LLC
Category: otc | Type: HUMAN OTC DRUG LABEL
Date: 20121114

ACTIVE INGREDIENTS: AVOBENZONE 1.5 g/50 mL; HOMOSALATE 4 g/50 mL; OCTINOXATE 3.75 g/50 mL; OCTISALATE 2.5 g/50 mL; OXYBENZONE 1.75 g/50 mL
INACTIVE INGREDIENTS: WATER; PPG-3 BENZYL ETHER MYRISTATE; BUTYLENE GLYCOL; CYCLOMETHICONE 5; TEA LEAF; GLYCERIN; CETYL ALCOHOL; DIMETHICONE; GLYCERYL MONOSTEARATE; VITAMIN A PALMITATE; DIETHYLHEXYL 2,6-NAPHTHALATE; DIPTERYX ODORATA SEED; SOYBEAN; DIMETHICONE/DIENE DIMETHICONE CROSSPOLYMER; PEG-75 STEARATE; CARBOMER INTERPOLYMER TYPE A (ALLYL SUCROSE CROSSLINKED) ; TETRAHEXYLDECYL ASCORBATE; CHLORPHENESIN; 1,2-HEXANEDIOL; CAPRYLYL GLYCOL; CETETH-20; STEARETH-20; POTASSIUM SORBATE; SODIUM BENZOATE; MICA; ASCORBIC ACID; SACCHAROMYCES LYSATE; SODIUM HYDROXIDE; UREA; SODIUM PYRROLIDONE CARBOXYLATE; SUNFLOWER OIL; TITANIUM DIOXIDE; EDETATE DISODIUM; PANTOTHENIC ACID; YEAST; XANTHAN GUM; CORN OIL; POLYQUATERNIUM-51 (2-METHACRYLOYLOXYETHYL PHOSPHORYLCHOLINE/N-BUTYL METHACRYLATE; 3:7) ; TREHALOSE; TOCOPHEROL; CYCLOMETHICONE 4; SODIUM ALGINATE; HYDROXYETHYL CELLULOSE (2000 MPA.S AT 1%) ; SODIUM CITRATE; HYALURONATE SODIUM; PHENOXYETHANOL; SODIUM CHLORIDE; SESAME OIL; POLYSORBATE 20; CITRIC ACID MONOHYDRATE; MACADAMIA OIL; OLIVE OIL; CERAMIDE 2; LECITHIN, SOYBEAN; METHYLISOTHIAZOLINONE; YEAST; ZINC; COPPER ; IRON; MAGNESIUM; SILICON; CORALLINA OFFICINALIS; PROPYLENE GLYCOL; TRIACETIN; METHYLPARABEN; CHLORELLA VULGARIS; RADISH; TROPOLONE; GARDEN CRESS SPROUT; MEDIUM-CHAIN TRIGLYCERIDES; LITCHI FRUIT; ETHYLPARABEN ; BUTYLPARABEN; SUGARCANE; BIOTIN; CRITHMUM MARITIMUM; ORANGE; LEMON; CITRAL; PALMITOYL OLIGOPEPTIDE; ACER SACCHARUM BARK/SAP; PALMITOYL TETRAPEPTIDE-7; VACCINIUM MYRTILLUS FRUITING TOP; ISOBUTYLPARABEN; PROPYLPARABEN

Active ingredients

Drug Facts

Active ingredients

Avobenzone 3.0%, Homosalate 8.0%, Octinoxate 7.5%, Octisalate 5.0%, Oxybenzone 3.5%

Purposes

Sunscreen

Keep out of reach of children. If swallowed get medical help or contact a Poison Control Center right away.

Uses

- helps prevent sunburn
- higher SPF gives more sunburn protection

Warnings

For external use only.

When using this product keep out of eyes. Rinse with water to remove.

Stop use and ask a doctor if rash or irritation develops and lasts.

Directions

- Apply generously and evenly 20 minutes before sun exposure
- Children under 6 months of age ask a doctor
- Reapply as needed or after towel drying, swimming, or prespiring

Other information

Reports of serious side effects associated with use of the product can be sent to : 75 Varick St. 10th floor New York, New York 10013

Inactive Ingredients

water, PPG -3 benzyl ether myristate, butylene glycol, cyclopentasiloxane, saccharomyces/xylin/black tea ferment, glycerin, cetyl alcohol, dimethicone, glyceryl stearate, retinyl palmitate/carrot polypeptide, diethylhexyl 2,6-naphthalate, lactobacillus/dipteryx odorata seed ferment filtrate, glycine soja (soybean) seed extract, dimethicone crosspolymer, PEG-75 stearate, carbomer, tetrahexydecyl ascorbate, chlorphenesin, 1,2-hexanediol, caprylyl glycol, ceteth-20, stearate-20, potassium sorbate, sodium benzoate, mica (cl 77019), sacorbic acid/orange citrus limon/citrus aurantifolia polypeptides, saccharomyces lysate extract, sodium hydroxide, urea, sodium PCA, helianthus annus (sunflower) seed oil, titanium dioxide (cl 77891), disodium EDTA, pantothenic acid/yeast polypeptide, xanthan gum, dimethylcyclosiloxane, zea mays (corn) oil, polyquaternium-51, trehalose, tocopherol/wheat polypeptide, cyclotetrasiloxane, hydroiyzed algin, hydroxyethylcellulose, fragrance(parfum), sodium citrate, sodium hyaluronate, phenoxyethanol, sea water, sesamum indicum(sesame) seed oil, polysorbate 20, citric acid, macadamia integrifolia seed oil, olea europaea (olive) fruit oil, ceramide 2, lecithin, methylisothiazolinone, saccharomycel/zinc ferment, saccharomyces/copper ferment, saccharomyces/iron ferment, saccharomyces/magnesium ferment, saccharomyces/silicon ferment, corallina officinalis extract, propylene glycol, triacetin, methylparaben, chlorella vulgaris extract, leuconostoc/radish root ferment filtrate, tropolone, lepidium sativum sprout extract, caprylic/capric triglyceride, litchi chinensis pericarp extract, ethylparaben, butylparaben, vaccinium myrtillus fruit/leaf extract, isobutylparaben, propylparaben, hydrogenated vegetable oil, saccharum officinarum (sugar cane) extract, biotin, cithmun maritimum extract, citrus aurantium dulcis (orange) fruit extract, citrus medica limonum (lemon fruit extract, citral, palmitoyl oligopeptide, acer saccharum (sugar maple) extract, palmitoyl tetrapeptide-7, titanium dioxide

Product Label

bliss

from our spa to your skin

THE YOUTH

AS WE KNOW IT

anti-aging moisture lotion

10 age-battling benefits with UVA/UVB sunscreen protection

spf 30

50mL/1.7fl oz

'SPA'-TACULAR RESULTS

We've poured the expertise behind our spa's THE YOUTH AS WE KNOW IT facial into this bottle, so you know you'll get spa-worthy results at home.

To book an appointment at Bliss Spa, click: blissworld.com or call: 877 TO BLISS

THIS 10-IN-1 TURN-BACK-TIME LOTION:

1 protects fron UVA and UVB rays

2 promoted collagen production

3 visibly diminishes wrinkles

4 visibly fills fine lines

5 helps increase cellular oxygenation

6 evens skin tone

7 hydrates, plumps and firms

8 replenishes and soothes

9 smoothes skin's texture

10 brightens and clarifies

bliss Dist. Bliss New York, NY 10013 USA London HA3 6DQ UK Made in USA - 1003-02262 blissworld.com